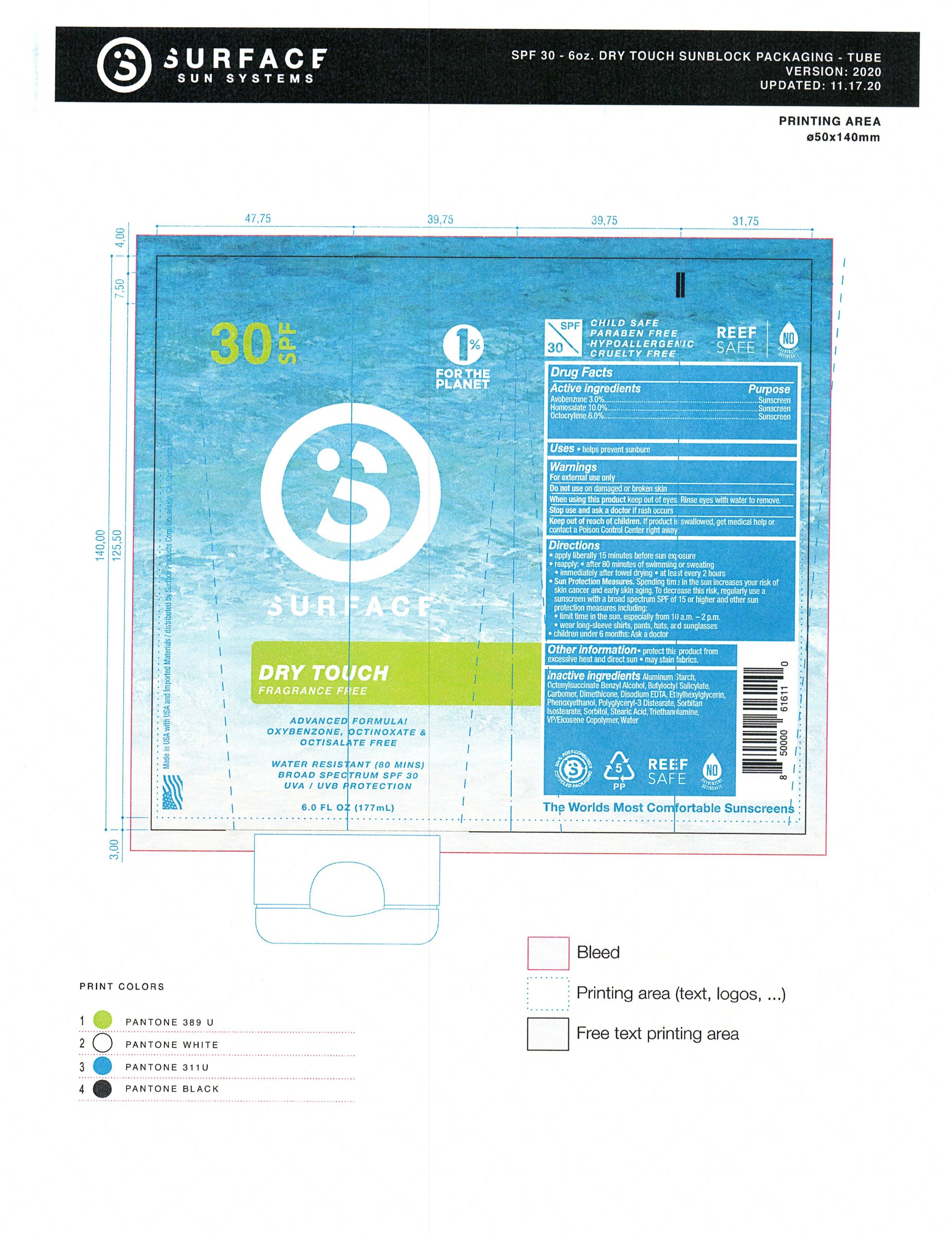 DRUG LABEL: Surface Dry Touch SPF 30 Sunscreen
NDC: 72344-104 | Form: LOTION
Manufacturer: Surface Products Corp
Category: otc | Type: HUMAN OTC DRUG LABEL
Date: 20260203

ACTIVE INGREDIENTS: AVOBENZONE 3 g/100 mL; OCTOCRYLENE 6 g/100 mL; HOMOSALATE 10 g/100 mL
INACTIVE INGREDIENTS: SORBITAN ISOSTEARATE; VINYLPYRROLIDONE/EICOSENE COPOLYMER; BUTYLOCTYL SALICYLATE; CARBOMER 934; TRIETHANOLAMINE 2-CYCLOHEXYL-4,6-DINITROPHENOLATE; ALUMINUM STARCH OCTENYLSUCCINATE; .ALPHA.-(.ALPHA.-AMINOPROPYL)BENZYL ALCOHOL HYDROCHLORIDE, ERYTHRO-(+/-)-; POLYGLYCERYL-3 DISTEARATE; EDETATE DISODIUM ANHYDROUS; WATER; DIMETHICONE 500; STEARIC ACID D7; SORBITOL; PHENOXYETHANOL; ETHYLHEXYLGLYCERIN

Surface Dry Touch SPF 30 Sunscreen Lotion

Active Ingredients

Avobenzone - 1.8%

Homosalate - 7.0%

Octocrylene - 5.0%

When using this product

• keep out of eyes. Rinse with water to remove.

• Keep away from face to avoid breathing it.

Uses

Avobenzone - 1.8% ................. Sunscreen

Homosalate - 7.0% .................. Sunscreen

Octocrylene - 5.0% ...................Sunscreen

Warnmings

Stop use and ask a doctor if rash occurs.

Warnings

Keep out of reach of children. If swallowed, get medical help or contact a Poison Control Center right away.

Inactive Ingredients

Aluminum Starch Octenylsuccinate

Benzyl Alcohol

Butyloctyl Salicylate

Carbomer

Dimethicone

Disodium EDTA

Methylparaben

Polyglyceryl-3 Distearate

Propylparaben

Sorbitan Isostearate

Sorbitol

Stearic Acid

Tocopherol

Triethanolamine

VP/Eicosene Copolymer

Water

WARNINGS

For external use only

Do not use on damaged or broken skin

when using this product keep out of eyes-rinse with water to remove

DOSAGE AND ADMINISTRATION

Apply liberally 15 minutews befor sun exposure

Reaaply:

- fter 80 monutes of swimming or sweating

- immediatly after towel drying

- at least every 2 hours

INDICATIONS AND USAGE

Helps prevent sunburn

Higher SPF gives more sunburn protection

If used as directed with other sun protection measures, decreases the reisk of skin cancer and early skim agingcaused by the s